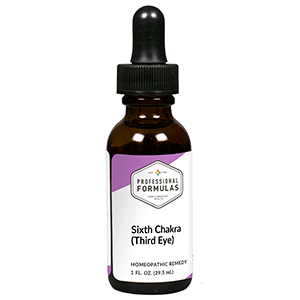 DRUG LABEL: Sixth Chakra (Third Eye)
NDC: 63083-7306 | Form: LIQUID
Manufacturer: Professional Complementary Health Formulas
Category: homeopathic | Type: HUMAN OTC DRUG LABEL
Date: 20190815

ACTIVE INGREDIENTS: MARSDENIA CUNDURANGO WHOLE 6 [hp_X]/29.5 mL; POTASSIUM PHOSPHATE, UNSPECIFIED FORM 8 [hp_X]/29.5 mL; SODIUM PHOSPHATE, DIBASIC, HEPTAHYDRATE 8 [hp_X]/29.5 mL; STRYCHNOS NUX-VOMICA SEED 8 [hp_X]/29.5 mL; SILICON DIOXIDE 8 [hp_X]/29.5 mL; SPIGELIA ANTHELMIA WHOLE 8 [hp_X]/29.5 mL; BUFO BUFO CUTANEOUS GLAND 12 [hp_X]/29.5 mL; LYCOSA TARANTULA 12 [hp_X]/29.5 mL; CORALLIUM RUBRUM EXOSKELETON 15 [hp_X]/29.5 mL; CALCIUM HEXAFLUOROSILICATE 30 [hp_X]/29.5 mL
INACTIVE INGREDIENTS: ALCOHOL; WATER

RCT6

ACTIVE INGREDIENTS

Condurango 6X
Kali phosphoricum 8X
Natrum phosphoricum 8X
Nux vomica 8X
Silicea 8X
Spigelia anthelmia 8X
Bufo rana 12X
Tarentula hispana 12X
Corallium rubrum 15X
Lapis lazuli 30X, 60X, 100X
Rose quartz 30X, 60X, 100X
Tiger's eye 30X, 60X, 100X

QUESTIONS

Professional Formulas

PO Box 2034 Lake Oswego, OR 97035

INDICATIONS

Temporarily relieves heightened skepticism, being judgmental or dismissive, being detached from others, not trusting ones self, being focused inward, fear of the unknown, sadness, indecisiveness, or procrastination.*

PURPOSE

*Claims based on traditional homeopathic practice, not accepted medical evidence. Not FDA evaluated.

WARNINGS

In case of overdose, get medical help or contact a poison control center right away.

Keep out of the reach of children.

PREGNANCY OR BREAST FEEDING

If pregnant or breastfeeding, ask a healthcare professional before use.

DIRECTIONS

Place drops under tongue 30 minutes before/after meals. Adults and children 12 years and over: Take 5 drops up to 4 times per day for up to one month. Consult a physician for use in children under 12 years of age.

OTHER INFORMATION

Tamper resistant. If seal is broken, do not use. After opening, close container tightly and store at room temperature away from heat.

INACTIVE INGREDIENTS

20% ethanol, purified water.

LABEL

Est 1985

Professional Formulas

Complementary Health

Sixth Chakra (Third Eye)

Homeopathic Remedy

1 FL. OZ. (29.5 mL)